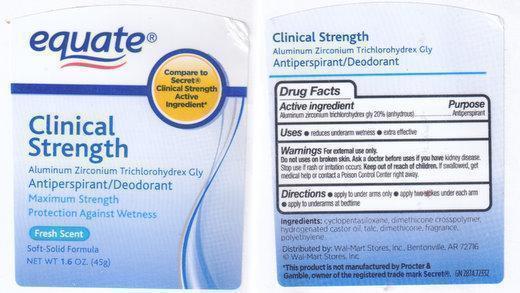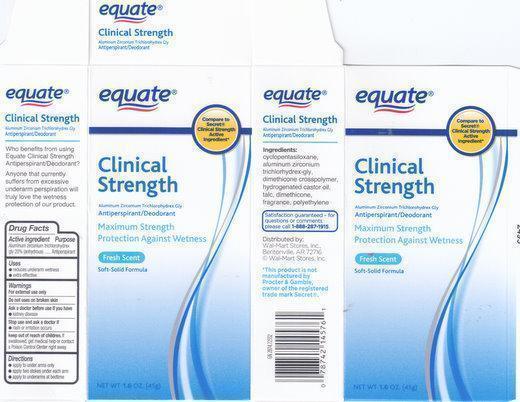 DRUG LABEL: EQUATE
NDC: 49035-917 | Form: STICK
Manufacturer: Wal-Mart Stores Inc
Category: otc | Type: HUMAN OTC DRUG LABEL
Date: 20111222

ACTIVE INGREDIENTS: ALUMINUM ZIRCONIUM TRICHLOROHYDREX GLY 200 mg/1 g
INACTIVE INGREDIENTS: CYCLOMETHICONE 5; HYDROGENATED CASTOR OIL; Talc; DIMETHICONE; DIMETHICONE; HIGH DENSITY POLYETHYLENE

ACTIVE INGREDIENT

Active Ingredients: Aluminum Zirconium Trichlorohydrex Gly 20% (anhydrous).

Purpose: Antiperspirant

Use

- Reduces underarm wetness
- extra effective

Warning:

For external use only.
Do not use on broken skin.

Ask a doctor before use if you have kidney disease.

Stop use if rash or irritation occurs

Keep out of reach of children.If swallowed, get medical help or contact a poison control center right away

DOSAGE AND ADMINISTRATION

- apply to under arms only
- apply two strokes under each arm
- apply to underarms at bedtime

INACTIVE INGREDIENT

Ingredients: Cyclopentasiloxane, Dimethicone crosspolymer, Hydrogenated Castor oil, Talc, Dimethicone, Polyethylene, Fragrance